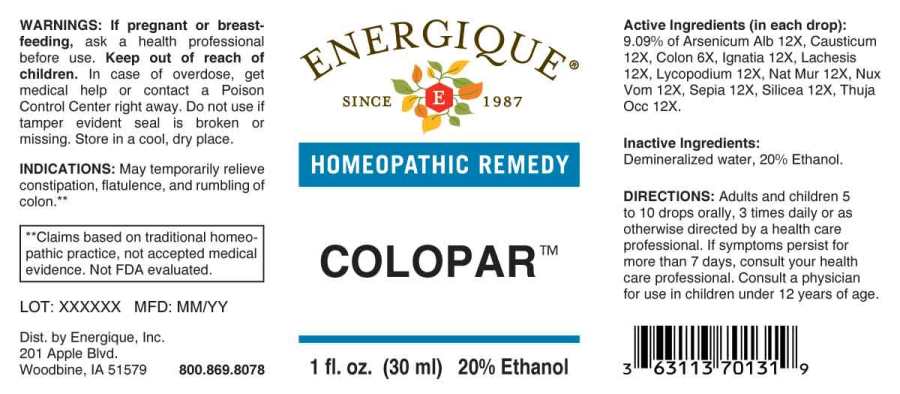 DRUG LABEL: Colopar
NDC: 44911-0331 | Form: LIQUID
Manufacturer: Energique, Inc.
Category: homeopathic | Type: HUMAN OTC DRUG LABEL
Date: 20240520

ACTIVE INGREDIENTS: SUS SCROFA COLON 6 [hp_X]/1 mL; ARSENIC TRIOXIDE 12 [hp_X]/1 mL; CAUSTICUM 12 [hp_X]/1 mL; STRYCHNOS IGNATII SEED 12 [hp_X]/1 mL; LACHESIS MUTA VENOM 12 [hp_X]/1 mL; LYCOPODIUM CLAVATUM SPORE 12 [hp_X]/1 mL; SODIUM CHLORIDE 12 [hp_X]/1 mL; STRYCHNOS NUX-VOMICA SEED 12 [hp_X]/1 mL; SEPIA OFFICINALIS JUICE 12 [hp_X]/1 mL; SILICON DIOXIDE 12 [hp_X]/1 mL; THUJA OCCIDENTALIS LEAFY TWIG 12 [hp_X]/1 mL
INACTIVE INGREDIENTS: WATER; ALCOHOL

DRUG FACTS:

ACTIVE INGREDIENTS:

(in each drop): 9.09% of Arsenicum Album 12X, Causticum 12X, Colon (Suis) 6X, Ignatia Amara 12X, Lachesis Mutus 12X, Lycopodium Clavatum 12X, Natrum Muriaticum 12X, Nux Vomica 12X, Sepia 12X, Silicea 12X, Thuja Occidentalis 12X.

INDICATIONS:

May temporarily relieve constipation, flatulence, and rumbling of colon.**

**Claims based on traditional homeopathic practice, not accepted medical evidence. Not FDA evaluated.

WARNINGS:

If pregnant or breastfeeding, ask a health professional before use.

Keep out of reach of children. In case of overdose, get medical help or contact a Poison Control Center right away.

Do not use if tamper evident seal is broken or missing.

Store in a cool, dry place.

KEEP OUT OF REACH OF CHILDREN:

In case of overdose, get medical help or contact a Poison Control Center right away.

DIRECTIONS:

Adults and children 5 to 10 drops orally, 3 times daily or as otherwise directed by a health care professional. If symptoms persist for more than 7 days, consult your health care professional. Consult a physician for use in children under 12 years of age.

INDICATIONS:

May temporarily relieve constipation, flatulence and rumbling of colon.**

**Claims based on traditional homeopathic practice, not accepted medical evidence. Not FDA evaluated.

INACTIVE INGREDIENTS:

Demineralized water, 20% Ethanol.

QUESTIONS:

Dist. by Energique, Inc.
201 Apple Blvd.
Woodbine, IA 51579 800.869.8078

PACKAGE LABEL DISPLAY:

ENERGIQUE
SINCE 1987
HOMEOPATHIC REMEDY
COLOPAR
1 fl. oz. (30 ml)